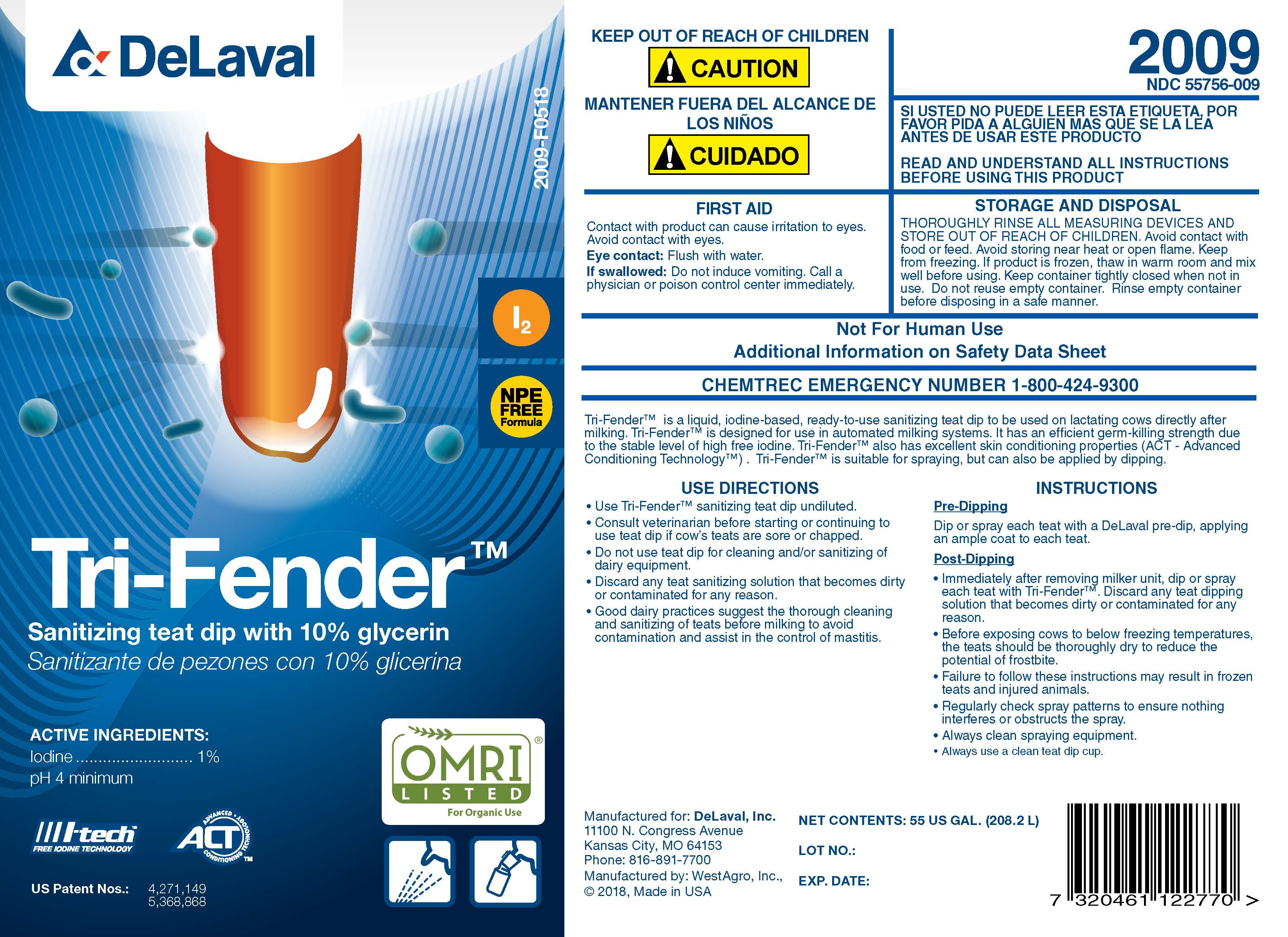 DRUG LABEL: Tri-Fender
NDC: 55756-009 | Form: SOLUTION
Manufacturer: DeLaval
Category: animal | Type: OTC ANIMAL DRUG LABEL
Date: 20211220

ACTIVE INGREDIENTS: IODINE I-120 10 g/1 kg
INACTIVE INGREDIENTS: SODIUM HYDROXIDE; ANHYDROUS CITRIC ACID; GLYCERIN; XANTHAN GUM; SODIUM IODIDE I-123; POLOXAMER 335; DOCUSATE SODIUM; SODIUM IODATE; WATER

DeLaval
Tri-Fender

INDICATIONS AND USAGE

I2

Sanitizing teat dip with 10% glycerin

Sanitizante de pezones con 10% glicerina

ACTIVE INGREDIENTS:

Iodine .................... 1%

pH 4 minimum

l-tech

FREE IODINE TECHNOLOGY

ACT

ADVANCED CONDITIONING TECHNOLOGY

US Patent Nos.: 4,271,149

5,368,868

2009-D0116

I2

NPE FREE Formula

KEEP OUT OF REACH OF CHILDREN

!CAUTION

MANTENER FUERA DEL ALCANCE DE LOS NINOS

!CUIDADO

FIRST AID

Contact with product can cause irritation to eyes.

Avoid contact with eyes.

Eye contact: Flush with water.

If swallowed: Do not induce vomiting. Call a physician or poison control center immediately.

2009

NDC 55756-009

SI USTED NO PUEDE LEER ESTA ETIQUETA, POR FAVOR PIDA A ALGUIEN MAS QUE SE LA LEA ANTES DE USAR ESTE PRODUCTO

READ AND UNDERSTAND ALL INSTRUCTIONS BEFORE USING THIS PRODUCT

STORAGE AND DISPOSAL

THOROUGHLY RINSE ALL MEASURING DEVICES AND STORE OUT OF REACH OF CHILDREN. Avoid contact with food or feed. Avoid storing near heat or open flame. Keep from freezing. If product is frozen, thaw in warm room and mix well before using. Keep container tightly closed when not in use. Do not reuse empty container. Rinse empty container before disposing in a safe manner.

Not for Human Use

Additional Information on Material Safety Data Sheet

CHEMTREC EMERGENCY NUMBER 1-800-424-9300

INDICATIONS AND USAGE

Tri-Fender is a liquid, iodine-based, ready-to-use sanitizing teat dip to be used on lactating cows directly after milking. Tri-Fender is designed for use in automated milking systems. It has an efficient germ-killing strength due to the stable level of high free iodine. Tri-Fender also has excellent skin conditining properties (ACT- Advanced Conditioning Technology). Tri-Fender is suitable for spraying, but can also be applied by dipping.

USE DIRECTIONS

- Use Tri-Fender santizing dip undiluted.
- Consult veterinarian before starting or continuing to use teat dip if cow's teats are sore or chapped.
- Do not use teat dip for cleaning and/or sanitizing of dairy equipment.
- Discard any teat sanitizing solution that becomes dirty or contaminated for any reason.
- Good dairy practices suggest the thorough cleaning and sanitizing of teats before milking to avoid contamination and assist in the control of mastitis.

INSTRUCTIONS

Pre-Dipping

Dip or spray each teat with a DeLaval pre-dip, applying an ample coat to each teat.

Post-Dipping

- Immediately after removing milker unit, dip or spray each teat with Tri-Fender. Discard any teat diping solution that becomes dirty or contaminated for any reason.
- Before exposing cows to below freezing temperatures, the teats should be thoroughly dry to reduce the potential of frostbite.
- Failure to follow these instructions may result in frozen teats and injured animals.
- Regularly check spray patterns to ensure nothing interferes or obstructs the spray.
- Always clean spraying equipment.
- Always use a clean teat dip cup.

Manufactured for: DeLaval, Inc.
11100 N. Congress Avenue
Kansas City, MO 64153
Phone: 816-891-7700
Manufactured by: WestAgro, Inc.
©2018, Made in USA

NET CONTENTS:

LOT NO.:

EXP. DATE: